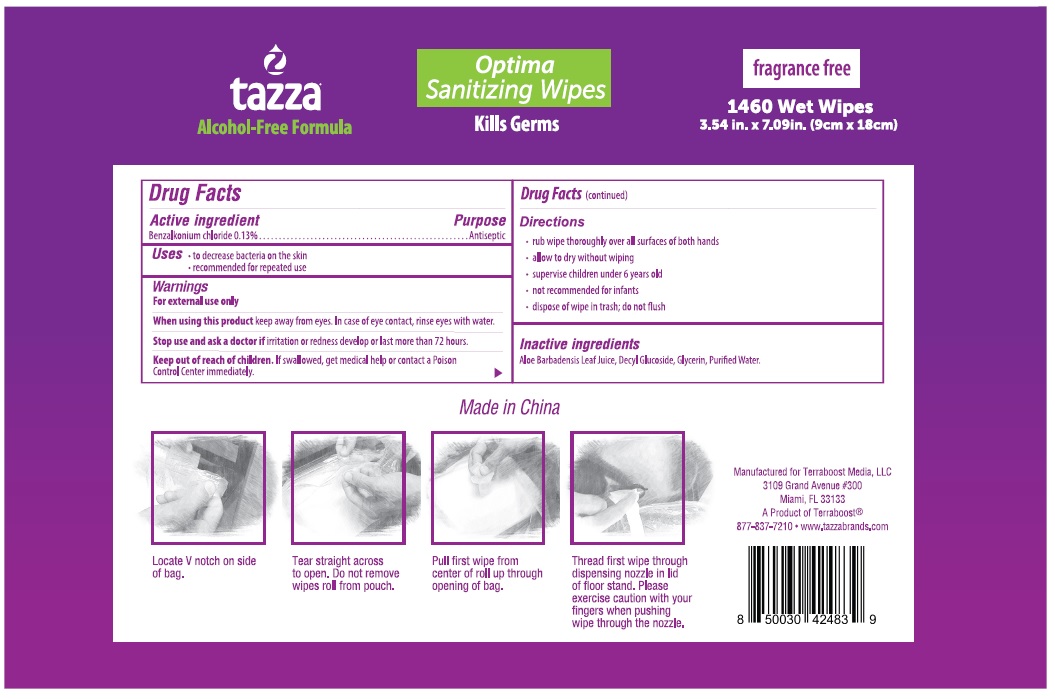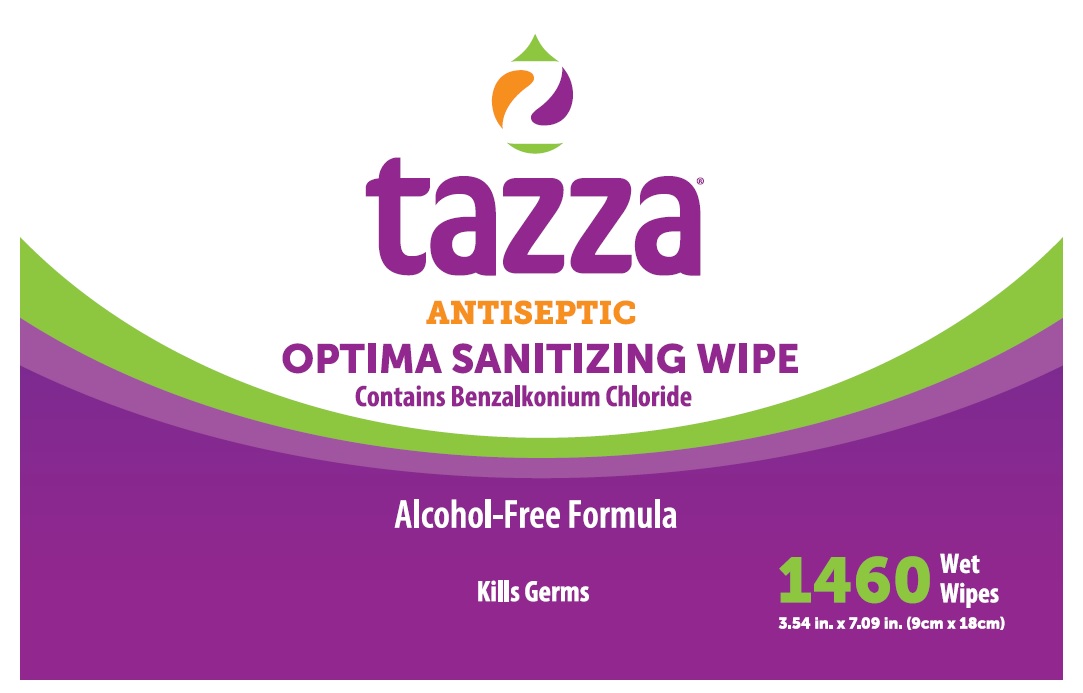 DRUG LABEL: Tazza Optima Sanitizing Wipes
NDC: 76370-0023 | Form: CLOTH
Manufacturer: Tazza Brands East Inc.
Category: otc | Type: HUMAN OTC DRUG LABEL
Date: 20240220

ACTIVE INGREDIENTS: BENZALKONIUM CHLORIDE 0.13 g/100 mL
INACTIVE INGREDIENTS: GLYCERIN; WATER; ALOE VERA LEAF; DECYL GLUCOSIDE

Tazza Optima Sanitizing Wipes – 1460ct

Drug Facts

Active ingredient

Benzalkonium Chloride 0.13%

Purpose

Antiseptic

Uses

- to decrease bacteria on the skin
- recommended for repeated use

Warnings

For external use only

When using this product keep away from eyes. In case of eye contact, rinse eyes with water.

Stop use and ask a doctor if irritation or redness develop or last more than 72 hours.

Keep out of reach of children. If swallowed, get medical help or contact a Poison Control Center immediately.

Directions

- rub wipe thoroughly over all surfaces of both hands
- allow to dry without wiping
- supervise children under 6 years old
- not recommended for infants
- dispose of wipe in trash, do not flush

INACTIVE INGREDIENT

Inactive ingredients Aloe Barbadensis Leaf Juice, Decyl Glucoside, Glycerin, Purified Water.

Manufactured for Terraboost Media, LLC
3109 Grand Avenue #300

Miami, FL 33133

A Product of Terraboost®

877-837-7210 • www.tazzabrands.com

Made in China

PACKAGE LABEL

tazza®

Antiseptic

OPTIMA SANITIZING WIPE

Contains Benzalkonium Chloride

Alcohol-Free Formula

Kills Germs

1460 Wet Wipes

3.54 in. x 7.09 in. (9cm x 18cm)